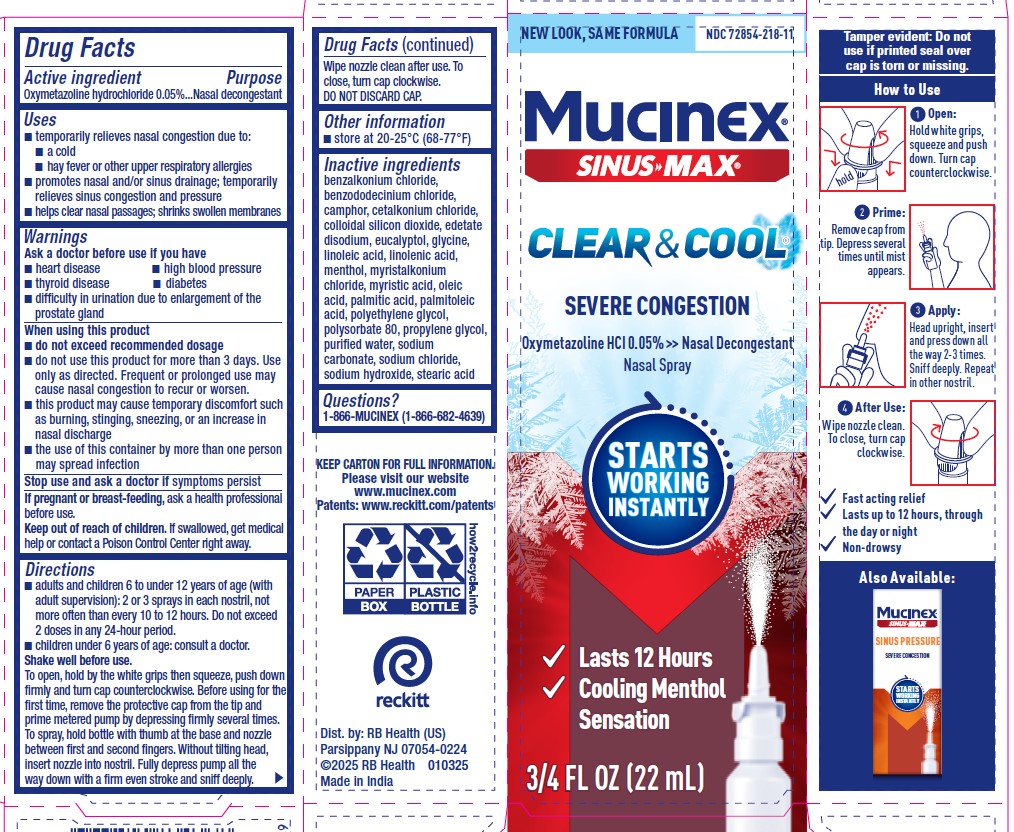 DRUG LABEL: Mucinex Sinus Max Clear and Cool Severe Congestion
NDC: 72854-218 | Form: SPRAY
Manufacturer: RB Health (US) LLC
Category: otc | Type: HUMAN OTC DRUG LABEL
Date: 20250224

ACTIVE INGREDIENTS: OXYMETAZOLINE HYDROCHLORIDE 0.05 g/100 mL
INACTIVE INGREDIENTS: CETALKONIUM CHLORIDE; EDETATE DISODIUM; EUCALYPTOL; LINOLEIC ACID; MENTHOL, UNSPECIFIED FORM; MYRISTIC ACID; OLEIC ACID; WATER; POLYETHYLENE GLYCOL, UNSPECIFIED; POLYSORBATE 80; SODIUM CHLORIDE; SODIUM HYDROXIDE; STEARIC ACID; MYRISTALKONIUM CHLORIDE; BENZALKONIUM CHLORIDE; BENZODODECINIUM CHLORIDE; CAMPHOR, (-)-; SILICON DIOXIDE; GLYCINE; PALMITIC ACID; PROPYLENE GLYCOL; LINOLENIC ACID; PALMITOLEIC ACID; SODIUM CARBONATE

Mucinex Sinus Max Clear & Cool Severe Congestion

Active ingredient
Oxymetazoline hydrochloride 0.05%

Purpose:

Nasal Decongestant

Uses
■ temporarily relieves nasal congestion due to:
■ a cold
■ hay fever or other upper respiratory allergies
■ promotes nasal and/or sinus drainage; temporarily
relieves sinus congestion and pressure
■ helps clear nasal passages; shrinks swollen membranes

Warnings
Ask a doctor before use if you have
■ heart disease

■ high blood pressure
■ thyroid disease

■ diabetes
■ difficulty in urination due to enlargement of the
prostate gland

When using this product
■ do not exceed recommended dosage
■ do not use this product for more than 3 days. Use
only as directed. Frequent or prolonged use may
cause nasal congestion to recur or worsen.
■ this product may cause temporary discomfort such
as burning, stinging, sneezing, or an increase in
nasal discharge
■ the use of this container by more than one person
may spread infection

Stop use and ask a doctor if symptoms persist

Directions
■ adults and children 6 to under 12 years of age (with
adult supervision): 2 or 3 sprays in each nostril, not
more often than every 10 to 12 hours. Do not exceed
2 doses in any 24-hour period.
■ children under 6 years of age: consult a doctor.

Shake well before use.
To open, hold by the white grips then squeeze, push down
firmly and turn cap counterclockwise. Before using for the
first time, remove the protective cap from the tip and
prime metered pump by depressing firmly several times.
To spray, hold bottle with thumb at the base and nozzle
between first and second fingers.Without tilting head,
insert nozzle into nostril. Fully depress pump all the
way down with a firm even stroke and sniff deeply.

Other information
■ store at 20-25°C (68-77°F)

Inactive ingredients
benzalkonium chloride,
benzododecinium chloride,
camphor, cetalkonium chloride,
colloidal silicon dioxide, edetate
disodium, eucalyptol, glycine,
linoleic acid, linolenic acid,
menthol, myristalkonium
chloride, myristic acid, oleic
acid, palmitic acid, palmitoleic
acid, polyethylene glycol,
polysorbate 80, propylene glycol,
purified water, sodium
carbonate, sodium chloride,
sodium hydroxide, stearic acid

Questions?
1-866-MUCINEX (1-866-682-4639)

PREGNANCY OR BREAST FEEDING

If pregnant or breast-feeding, ask a health professional
before use.
Keep out of reach of children. If swallowed, get medical
help or contact a Poison Control Center right away.

Keep out of reach of children. If swallowed, get medical
help or contact a Poison Control Center right away.